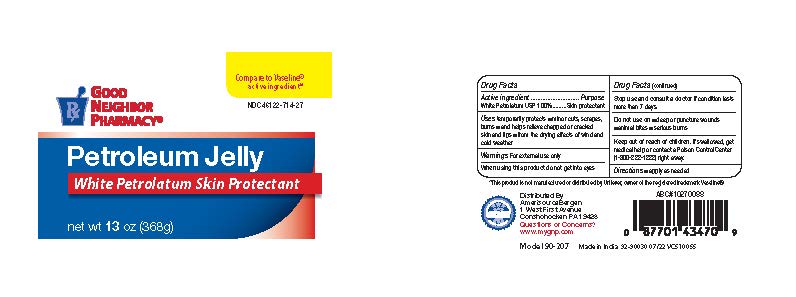 DRUG LABEL: Good Neighbor Petroleum Jelly
NDC: 46122-714 | Form: JELLY
Manufacturer: AmerisourceBergen
Category: otc | Type: HUMAN OTC DRUG LABEL
Date: 20251222

ACTIVE INGREDIENTS: PETROLATUM 100 g/100 g
INACTIVE INGREDIENTS: WATER

Good Neighbor Petroleum Jelly

Drug Facts

ACTIVE INGREDIENT

White Petroleum USP 100%

Active ingredients | Purpose
White Petrolatum 100% | Skin Protectant

Uses

- helps protect chapped or cracked skin and lips

Warnings

For external use only

When using this product

- do not get into eyes

Stop use and ask a doctor if

- if the condition lasts more than 7 days

Do not use on

- deep or puncture wounds .
- animal bites
- serious burns .

Keep out of reach of children.If swallowed, get medical help or contact a Poison Control Center (1-800-222-1222) right away.

Directions

Apply as needed

Inactive ingredient

Water